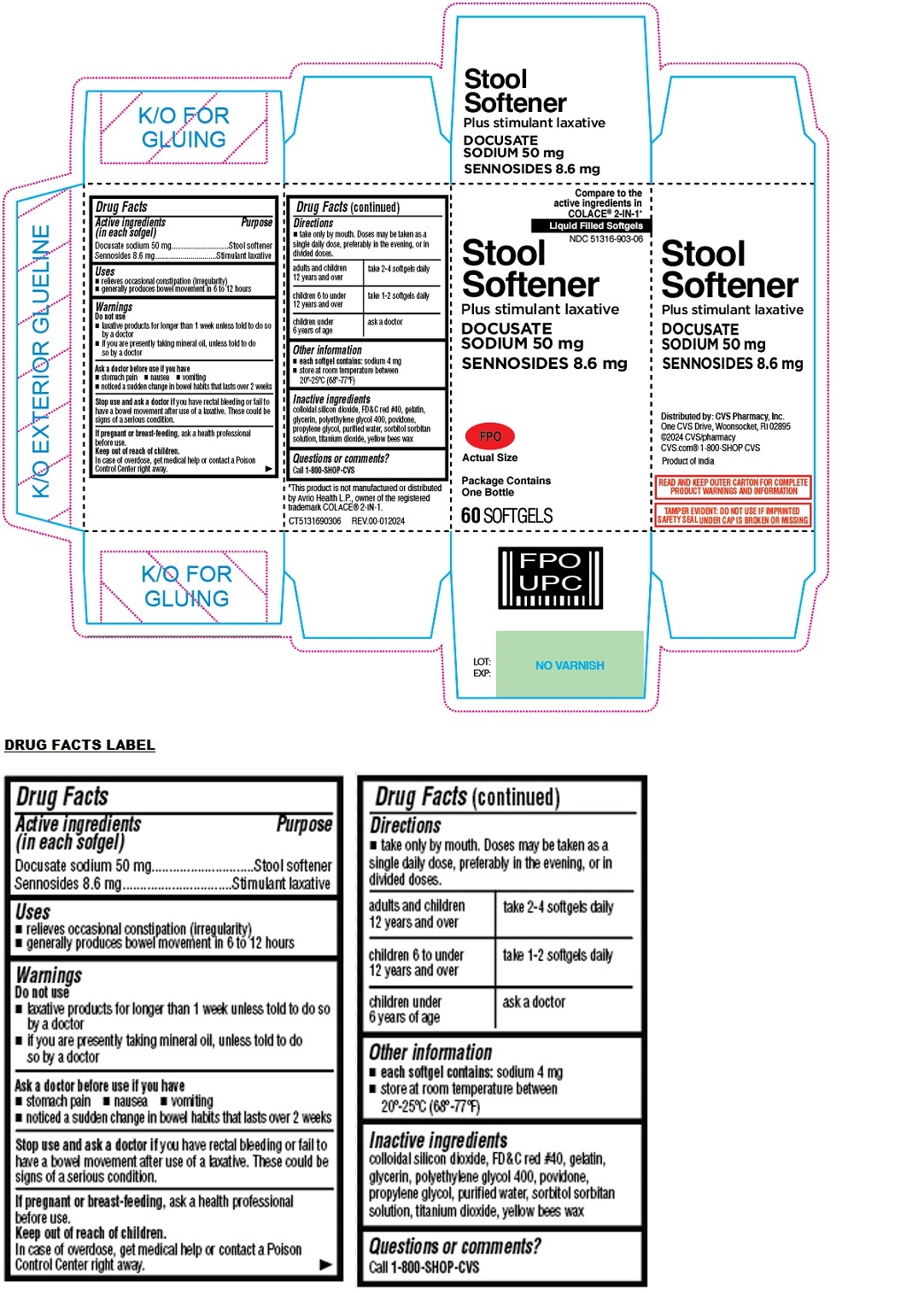 DRUG LABEL: CVS Health Stool Softener Plus stimulant laxative SOFTGEL
NDC: 51316-903 | Form: CAPSULE, LIQUID FILLED
Manufacturer: CVS Pharmacy, Inc.
Category: otc | Type: HUMAN OTC DRUG LABEL
Date: 20240118

ACTIVE INGREDIENTS: DOCUSATE SODIUM 50 mg/1 1; SENNOSIDES 8.6 mg/1 1
INACTIVE INGREDIENTS: SILICON DIOXIDE; FD&C RED NO. 40; GELATIN, UNSPECIFIED; GLYCERIN; POLYETHYLENE GLYCOL 400; POVIDONE, UNSPECIFIED; PROPYLENE GLYCOL; WATER; SORBITOL; SORBITAN; TITANIUM DIOXIDE; YELLOW WAX

CVS Health Stool Softener Plus stimulant laxative SOFTGEL

Active ingredients (in each softgel)

Docusate sodium 50 mg
Sennosides 8.6 mg

Purpose

Stool softener
Stimulant laxative

Uses

• relieves occasional constipation (irregularity)
• generally produces bowel movement in 6 to 12 hours

Warnings

Do not use
• laxative products for longer than 1 week unless told to do so by a doctor • if you are presently taking mineral oil, unless told to do so by a doctor

Ask a doctor before use if you have
• stomach pain • nausea • vomiting • noticed a sudden change in bowel habits that lasts over 2 weeks

Stop use and ask a doctor if you have rectal bleeding or fail to have a bowel movement after use of a laxative. These could be signs of a serious condition.

If pregnant or breast-feeding, ask a health professional before use.

Keep out of reach of children.
In case of overdose, get medical help or contact a Poison Control Center right away.

Directions

• take only by mouth. Doses may be taken as a single daily dose, preferably in the evening, or in divided doses.

adults and children 12 years and over | take 2-4 softgels daily
children 6 to under 12 years and over | take 1-2 softgels daily
children under 6 years of age | ask a doctor

Other information

• each softgel contains: sodium 4 mg
• store at room temperature between 20°-25°C (68°-77°F)

Inactive ingredients

colloidal silicon dioxide, FD&C red #40, gelatin, glycerin, polyethylene glycol 400, povidone, propylene glycol, purified water, sorbitol sorbitan solution, titanium dioxide, yellow bees wax

Questions or comments?

Call 1-800-SHOP-CVS

Compare to the active ingredients in COLACE® 2-IN-1*

Liquid Filled Softgels

Package Contains One Bottle

Distributed by: CVS Pharmacy, Inc.
One CVS Drive, Woonsocket, RI 02895
©2024 CVS/pharmacy
CVS.com® 1-800-SHOP CVS

Product of India

READ AND KEEP OUTER CARTON FOR COMPLETE PRODUCT WARNINGS AND INFORMATION

TAMPER EVIDENT: DO NOT USE IF IMPRINTED SAFETY SEAL UNDER CAP IS BROKEN OR MISSING

*This product is not manufactured or distributed by Avrio Health L.P., owner of the registered trademark COLACE® 2-IN-1.